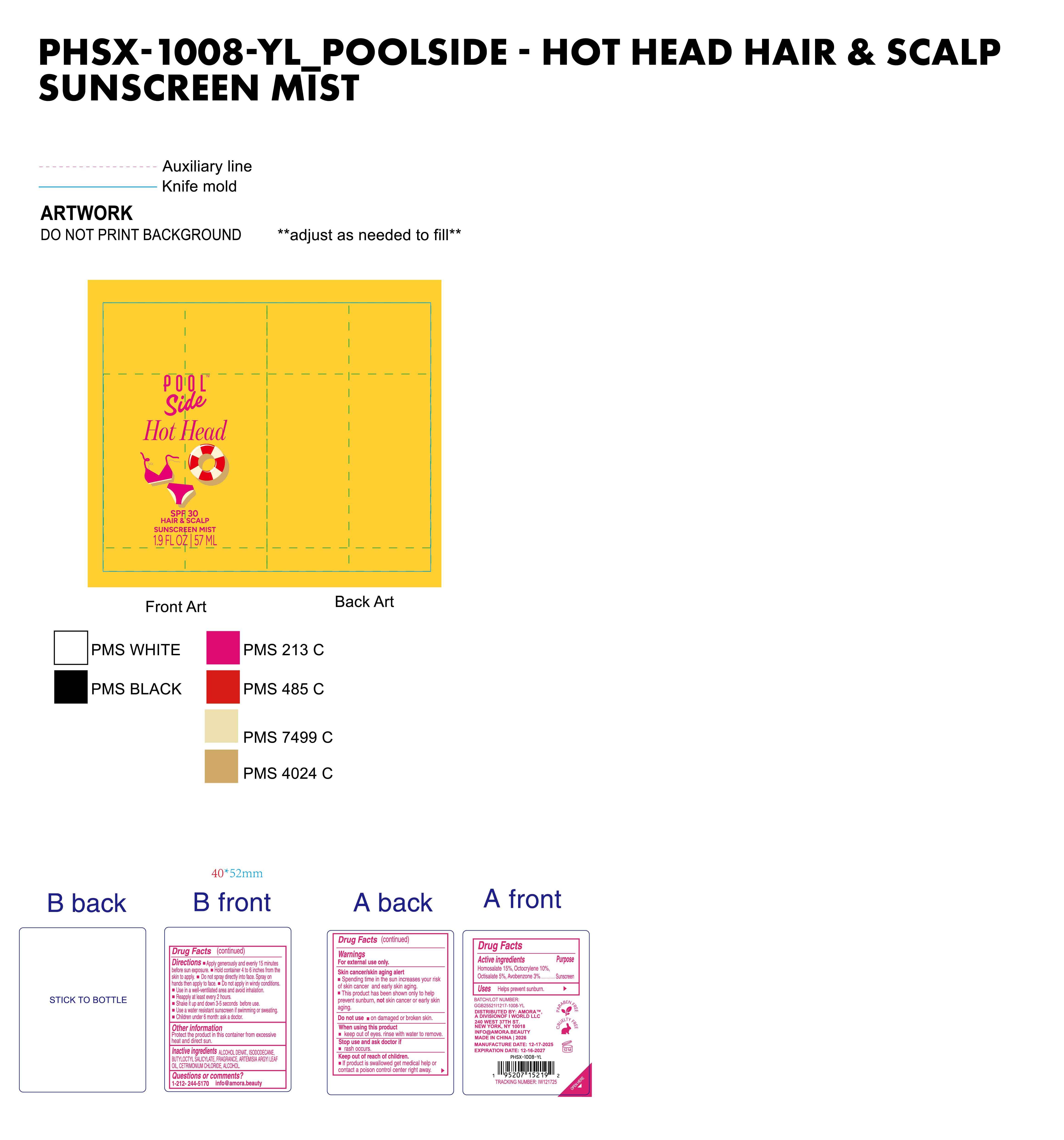 DRUG LABEL: Poolside Hot Head SPF 30 hair scalp sunscreen mist
NDC: 85161-142 | Form: SPRAY
Manufacturer: Longway Technology(Guangzhou)Co.,Ltd.
Category: otc | Type: HUMAN OTC DRUG LABEL
Date: 20251203

ACTIVE INGREDIENTS: OCTISALATE 0.05 g/1 mL; HOMOSALATE 0.15 g/1 mL; OCTOCRYLENE 0.1 g/1 mL; AVOBENZONE 0.03 g/1 mL
INACTIVE INGREDIENTS: ALCOHOL; BUTYLOCTYL SALICYLATE; CETRIMONIUM CHLORIDE; ARTEMISIA ARGYI LEAF; ISODODECANE; FRAGRANCE 13576

ACTIVE INGREDIENT

Homosalate 15%, Octocrylene 10%, Octisalate 5% , Avobenzone 3%

PURPOSE

sunscreen

Keep out of reach of children.

lf product is swallowed get medical help or contact a poison control center right away.

Warnings

For external use only.

Skin cancer/skin aging alert

Spending time in the sun increases your risk of skin cancer and early skin aging.

This product has been shown only to help prevent sunburn, not skin cancer or early skin aging.

Do not use on damaged or broken skin.

When using this product

keep out of eyes. rinse with water to remove

Stop use and ask doctor if

rash occurs.

Keep out of reach of children.

lf product is swallowed get medical help or contact a poison control center right away.

INDICATIONS AND USAGE

Helps prevent sunburn.

INACTIVE INGREDIENT

ALCOHOL DENAT, ISODODECANE ,BUTYLOCTYL SALICYLATE , FRAGRANCE , ARTEMISIA ARGYILEAF OIL, CETRIMONIUM CHLORIDE , ALCOHOL

OTHER SAFETY INFORMATION

Protect the product in this container from excessive heat and direct sun.

QUESTIONS

1-212-244-5170 info@amora.beauty

DirectionS

Apply generously and evenly 15 minutes before sun exposure.

Hold container 4 to 6 inches from the skin to apply.

Do not spray directly into face.

Spray on hands then apply to face.

Do not apply in windy conditions.

Use in a well-ventilated area and avoid inhalation.

Reapply at least every 2 hours.

Shake it up and down 3-5 seconds before use.

Use a water resistant sunscreen if swimming or sweating.

Children under 6 month: ask a doctor.